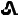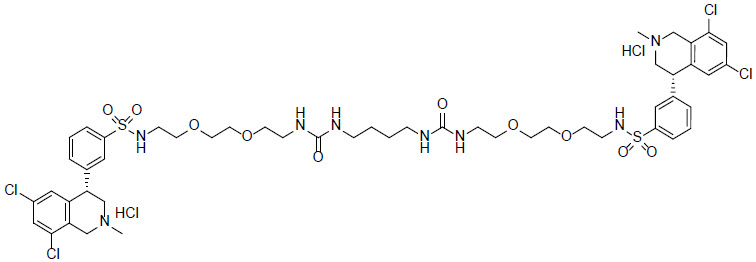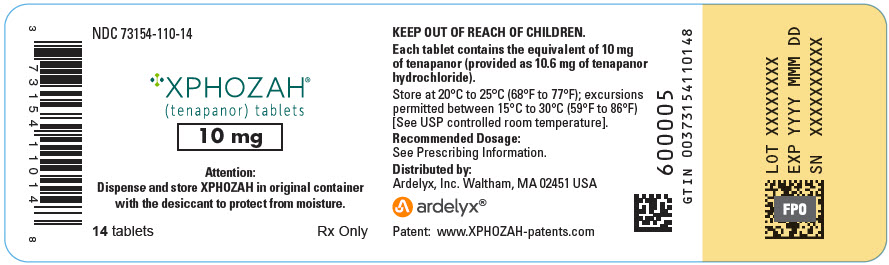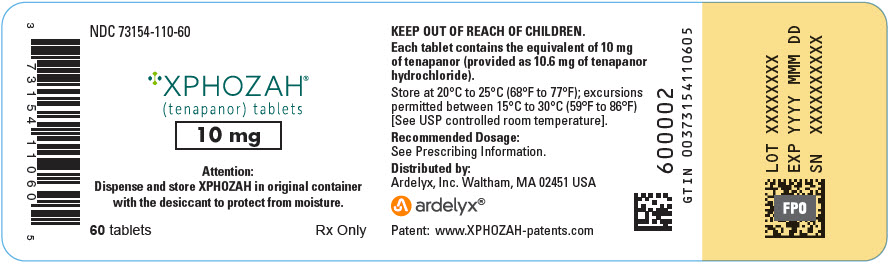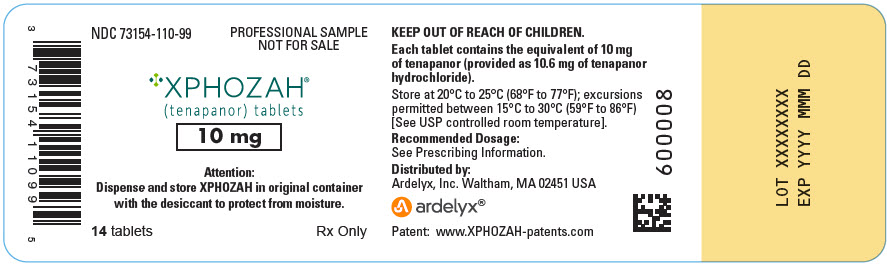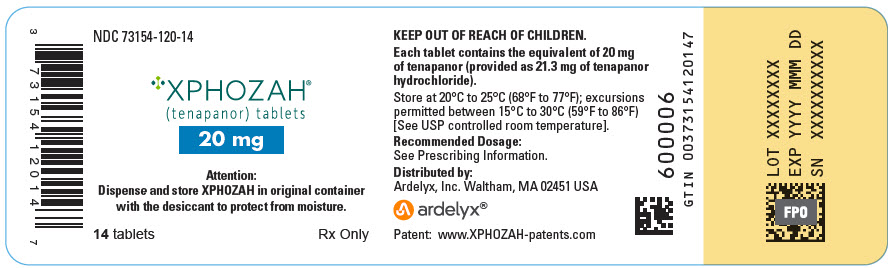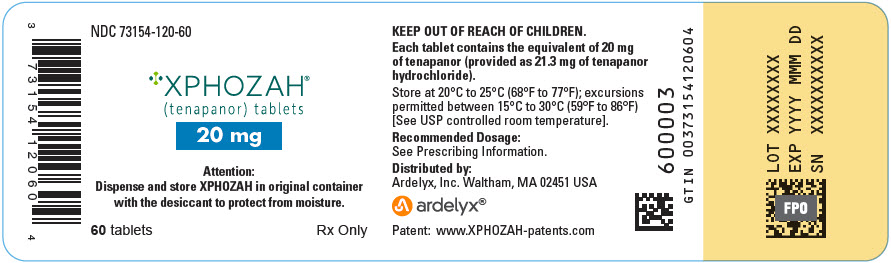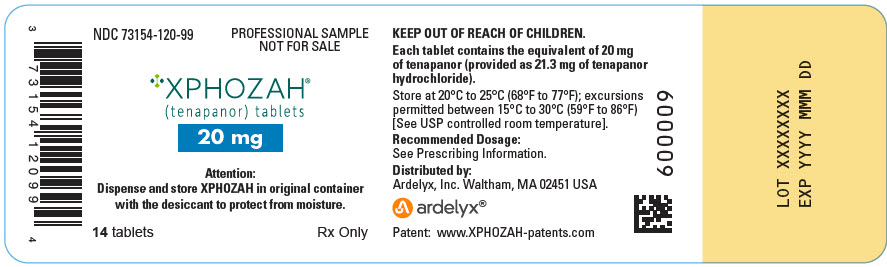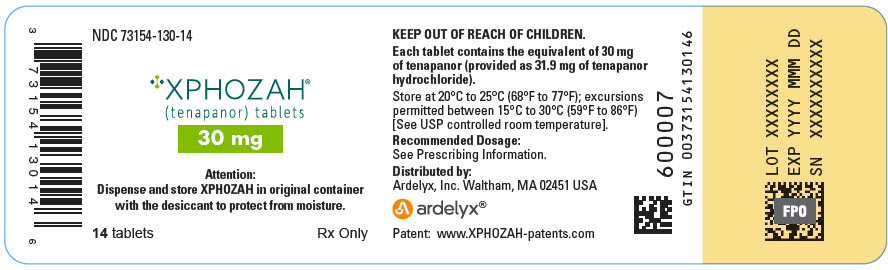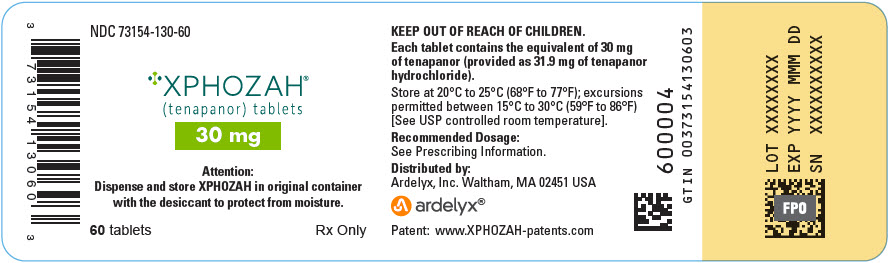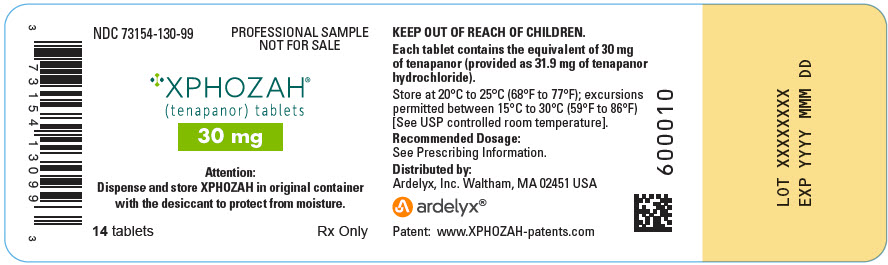 DRUG LABEL: XPHOZAH 10 mg
NDC: 73154-110 | Form: TABLET, FILM COATED
Manufacturer: Ardelyx, Inc.
Category: prescription | Type: HUMAN PRESCRIPTION DRUG LABEL
Date: 20250627

ACTIVE INGREDIENTS: TENAPANOR HYDROCHLORIDE 10 mg/1 1

HIGHLIGHTS OF PRESCRIBING INFORMATION

These highlights do not include all the information needed to use XPHOZAH® safely and effectively. See full prescribing information for XPHOZAH.
XPHOZAH (tenapanor) tablets, for oral use
Initial U.S. Approval: 2019

1 INDICATIONS AND USAGE

XPHOZAH is a sodium hydrogen exchanger 3 (NHE3) inhibitor indicated to reduce serum phosphorus in adults with chronic kidney disease (CKD) on dialysis as add-on therapy in patients who have an inadequate response to phosphate binders or who are intolerant of any dose of phosphate binder therapy (1).

2 DOSAGE AND ADMINISTRATION

- Recommended dosage: 30 mg orally twice daily before the morning and evening meals (2.1).
- Manage serum phosphorus levels and tolerability with dosage adjustments (2.1).
- Take just prior to the first and last meals of the day (2.2).
- Instruct patients not to take right before a hemodialysis session, and instead take right before the next meal following dialysis (2.2).

3 DOSAGE FORMS AND STRENGTHS

Tablets: 10 mg, 20 mg, 30 mg (3).

4 CONTRAINDICATIONS

Pediatric patients under 6 years of age (4).

Patients with known or suspected mechanical gastrointestinal obstruction (4).

5 WARNINGS AND PRECAUTIONS

Patients may experience severe diarrhea (5.1).

6 ADVERSE REACTIONS

Most common adverse reaction in the combined clinical trials was diarrhea, reported by 43-53% of patients (6).

To report SUSPECTED ADVERSE REACTIONS, contact Ardelyx at 1-844-974-6924 or FDA at 1-800-FDA-1088 or www.fda.gov/medwatch.

7 DRUG INTERACTIONS

- OATP2B1 Substrates: Potential for reduced exposure of the concomitant drug (e.g., enalapril). Monitor for signs related to loss of efficacy and adjust the dosage of the concomitantly administered drug as needed (7.1).
- Sodium Polystyrene Sulfonate (SPS): Separate administration by at least three hours (7.2).

FULL PRESCRIBING INFORMATION

1 INDICATIONS AND USAGE

XPHOZAH is indicated to reduce serum phosphorus in adults with chronic kidney disease (CKD) on dialysis as add-on therapy in patients who have an inadequate response to phosphate binders or who are intolerant of any dose of phosphate binder therapy.

2 DOSAGE AND ADMINISTRATION

2.1 Recommended Dosage

The recommended dosage is 30 mg orally twice daily before the morning and evening meals. Monitor serum phosphorus and adjust the dosage as needed to manage gastrointestinal tolerability.

2.2 Administration Instructions

- Instruct patients to take XPHOZAH just prior to the first and last meals of the day [see Clinical Pharmacology (12.2)].
- Instruct patients not to take XPHOZAH right before a hemodialysis session, and instead take right before the next meal following dialysis, as patients may experience diarrhea after taking XPHOZAH [see Warnings and Precautions (5.1)].
- Instruct patients who miss a dose to skip the missed dose and take the next dose at the regular time.

3 DOSAGE FORMS AND STRENGTHS

XPHOZAH tablets available as:

- 10 mg tenapanor supplied as a yellow, oval, biconvex film-coated tablet debossed with "" on one side and "T10" on the other side.
- 20 mg tenapanor supplied as a brown, oval, biconvex film-coated tablet debossed with "" on one side and "T20" on the other side.
- 30 mg tenapanor supplied as a red, oval, biconvex film-coated tablet debossed with "" on one side and "T30" on the other side.

4 CONTRAINDICATIONS

XPHOZAH is contraindicated in patients under 6 years of age because of the risk of diarrhea and serious dehydration [see Warnings and Precautions (5.1), Use in Specific Populations (8.5)].

XPHOZAH is contraindicated in patients with known or suspected mechanical gastrointestinal obstruction.

5 WARNINGS AND PRECAUTIONS

5.1 Diarrhea

Diarrhea was the most common adverse reaction in XPHOZAH-treated patients with CKD on dialysis [see Dosage and Administration (2), Contraindications (4) and Adverse Reactions (6.1)]. In clinical trials, diarrhea was reported in up to 53% of patients, reported as severe in 5%, and associated with dehydration and hyponatremia in less than 1% of patients. Treatment with XPHOZAH should be discontinued in patients who develop severe diarrhea.

6 ADVERSE REACTIONS

6.1 Clinical Trial Experience

Because clinical trials are conducted under widely varying conditions, adverse reaction rates observed in the clinical trials of a drug cannot be directly compared with rates in the clinical trials of another drug and may not reflect the rates observed in practice.

The safety data described below reflect data from 754 adults with CKD on dialysis taking XPHOZAH in clinical trials as monotherapy and in combination with phosphate binders. Among the 754 patients, 258 patients were exposed to tenapanor for at least 26 weeks and 75 were exposed to tenapanor for at least one year. [see Clinical Studies (14)].

Most Common Adverse Reaction

Diarrhea, which occurred in 43-53% of patients, was the only adverse reaction reported in at least 5% of XPHOZAH-treated patients with CKD on dialysis across trials. The majority of diarrhea events in the XPHOZAH-treated patients were reported to be mild-to-moderate in severity and resolved over time, or with dose reduction. Diarrhea was typically reported soon after initiation but could occur at any time during treatment with XPHOZAH. Severe diarrhea was reported in 5% of XPHOZAH-treated patients in these trials [see Warnings and Precautions (5.1)].

6.2 Postmarketing Experience

The following adverse reactions have been identified during post approval use of XPHOZAH. Because these reactions are reported voluntarily from a population of uncertain size, it is not always possible to reliably estimate their frequency or establish a causal relationship to drug exposure.

Hypersensitivity reactions: pruritis, rash, and urticaria

7 DRUG INTERACTIONS

7.1 OATP2B1 Substrates

Tenapanor is an inhibitor of intestinal uptake transporter, OATP2B1 [see Clinical Pharmacology (12.3)]. Drugs which are substrates of OATP2B1 may have reduced exposures when concomitantly taken with XPHOZAH. Monitor for signs related to loss of efficacy and adjust the dose of concomitantly administered drug as needed.

Enalapril is a substrate of OATP2B1. When enalapril was coadministered with XPHOZAH (30 mg twice daily for five days), the peak exposure (Cmax) of enalapril and its active metabolite, enalaprilat, decreased by approximately 70% and total systemic exposures (AUC) decreased by 50 to 65% compared to when enalapril was administered alone [see Clinical Pharmacology (12.3)]. However, the decrease in enalaprilat's exposure with XPHOZAH may be offset by the inherently higher exposures observed in patients with CKD on dialysis due to its reduced renal clearance. Therefore, a lower starting dose of enalapril, which is otherwise recommended in patients with CKD on dialysis is not required when enalapril is coadministered with XPHOZAH.

7.2 Sodium Polystyrene Sulfonate

Separate administration of XPHOZAH and sodium polystyrene sulfonate (SPS) by at least 3 hours. SPS binds to many commonly prescribed oral medicines.

8 USE IN SPECIFIC POPULATIONS

8.1 Pregnancy

Risk Summary

Tenapanor is essentially non-absorbed systemically, with plasma concentrations below the limit of quantification (less than 0.5 ng/mL) following oral administration [see Clinical Pharmacology (12.3)]. Therefore, maternal use is not expected to result in fetal exposure to the drug.

The available data on XPHOZAH exposure from a small number of pregnant women have not identified any drug associated risk for major birth defects, miscarriage, or adverse maternal or fetal outcomes. In reproduction studies with tenapanor in pregnant rats and rabbits, no adverse fetal effects were observed in rats at 0.2 times the maximum recommended human dose and in rabbits at doses up to 15 times the maximum recommended human dose (based on body surface area) [see Nonclinical Toxicology (13.1)].

The estimated background risk of major birth defects and miscarriage for women with CKD on dialysis with hyperphosphatemia is unknown. All pregnancies have a background risk of birth defect, loss, or other adverse outcomes. In the United States general population, the estimated background risk of major birth defects and miscarriage in clinically recognized pregnancies is 2% to 4% and 15% to 20%, respectively.

Animal Data

In an embryofetal development study in rats, tenapanor was administered orally to pregnant rats during the period of organogenesis at dose levels of 1, 10 and 30 mg/kg/day. Tenapanor doses of 10 and 30 mg/kg/day were not tolerated by the pregnant rats and was associated with mortality and moribundity with body weight loss. The 10 and 30 mg/kg dose group animals were sacrificed early, and the fetuses were not examined for intrauterine parameters and fetal morphology. No adverse fetal effects were observed in rats at 1 mg/kg/day (approximately 0.2 times the maximum recommended human dose) and in rabbits at doses up to 45 mg/kg/day (approximately 15 times the maximum recommended human dose, based on body surface area). In a pre- and post-natal developmental study in mice, tenapanor at doses up to 200 mg/kg/day (approximately 16.5 times the maximum recommended human dose, based on body surface area) had no effect on pre- and post-natal development.

8.2 Lactation

Risk Summary

Tenapanor and its major metabolite, M1, were not detected in the breast milk of lactating women (see Data). In adults, concentrations of tenapanor were below the limit of quantitation in plasma following multiple doses of tenapanor [see Clinical Pharmacology (12.3)]. Maternal use of XPHOZAH is not expected to result in exposure to tenapanor or its major metabolite in breastfed infants. There is no information on the effects of tenapanor or M1 on milk production. The developmental and health benefits of breastfeeding should be considered along with the mother’s clinical need for XPHOZAH and any potential adverse effects on the breastfed infant from XPHOZAH or from the underlying maternal condition.

Data

A clinical lactation study was conducted in seven healthy adult women who were 22 to 37 years of age. Following oral administration of tenapanor 50 mg twice daily for 3 days, the concentrations of tenapanor and its major metabolite were below the limit of quantitation (<1 ng/mL and <1 ng/mL) in all breast milk samples collected over 24 hours post dosing.

8.4 Pediatric Use

Risk Summary

XPHOZAH is contraindicated in patients less than 6 years of age. In nonclinical studies, deaths occurred in young juvenile rats (less than 1-week old rats; approximate human age-equivalent of less than 2 years of age) and in older juvenile rats (approximate human age-equivalent of 2 years of age) following oral administration of tenapanor, as described below in Juvenile Animal Toxicity Data.

The safety and effectiveness of XPHOZAH in pediatric patients have not been established.

Juvenile Animal Toxicity Data

In a 21-day oral dose range finding toxicity study in juvenile rats, tenapanor was administered to neonatal rats (post-natal day (PND) 5) at doses of 5 and 10 mg/kg/day. Tenapanor was not tolerated in male and female pups and the study was terminated on PND 16 due to mortalities and decreased body weight (24% to 29% reduction in females at the respective dose groups and 33% reduction in males in the 10 mg/kg/day group, compared to control).

In a second dose range finding study, tenapanor doses of 0.1, 0.5, 2.5, or 5 mg/kg/day were administered to neonatal rats from PND 5 through PND 24. Treatment-related mortalities were observed at 0.5, 2.5, and 5 mg/kg/day doses. These premature deaths were observed as early as PND 8, with majority of deaths occurring between PND 15 and 25. In the 5 mg/kg/day group, mean body weights were 47% lower for males on PND 23 and 35% lower for females on PND 22 when compared to the controls. Slightly lower mean tibial lengths (5% to 11%) were noted in males and females in the 0.5, 2.5, and 5 mg/kg/day dose groups on PND 25 and correlated with the decrements in body weight noted in these groups. Lower spleen, thymus, and/or ovarian weights were noted at the 0.5, 2.5, and 5 mg/kg/day doses. Tenapanor-related gastrointestinal distension and microscopic bone findings of increased osteoclasts, eroded bone, and/or decreased bone in sternum and/or femorotibial joint were noted in males and females in the 0.5, 2.5, and 5 mg/kg/day dose groups.

In juvenile rats administered tenapanor at 0.03, 0.1, or 0.3 mg/kg/day on PND 5 through PND 61, treatment-related mortalities were observed at 0.3 mg/kg/day. Lower mean body weight gains were noted in the 0.3 mg/kg/day group males and females compared to the control group primarily during PND 12–24 but continuing sporadically during the remainder of the dosing period; corresponding lower mean food consumption was noted in this group during PND 21–33. As a result, mean body weights were up to 15.8% and 16.8% lower in males and females, respectively, compared to the control group; the greatest difference was on PND 24 for males and PND 21 for females. Mean body weight in the 0.3 mg/kg/day group males was only 3.9% lower than the control group on PND 61. There were no tenapanor-related effects on mean body weights, body weight gains, or food consumption in the 0.03 and 0.1 mg/kg/day group males and females. A dosage level of 0.1 mg/kg/day was considered to be the no-observed-adverse-effect level (NOAEL) for juvenile toxicity of tenapanor [see Contraindications (4), Warnings and Precautions (5.1)].

In a 21-day oral dose range finding study in older (weaned) juvenile rats administered tenapanor at 0.1, 1, or 5 mg/kg/day on PND 21 through PND 41 (approximate human age-equivalent of 2 to 12 years of age), treatment-related mortalities or moribundities were observed during the first two days of the study in the 1 mg/kg/day males and the 5 mg/kg/day males and females. Watery feces, decreased food consumption, and lower mean body weight were also observed in the 1 and 5 mg/kg/day groups.

In weaned juvenile rats administered tenapanor at 0.1, 0.3, and 0.7 (males) or 1 (females) mg/kg/day on PND 21 through PND 80, no mortalities were observed. Significant decreases in mean body weights were observed in the 0.3 and 0.7 mg/kg/day males throughout the dosing period (up to 20.3% lower than control) and in the 1 mg/kg/day females between PND 23 to 35 (up to 16.7% lower than control), with food consumption notably decreased on PND 21 to 29. There were also reductions in tibia length between PND 76 and 80 in the 0.3 and 0.7 mg/kg/day males, and between PND 36 and 64 in the 0.7 mg/kg/day males, which were not observed during the 14-day recovery period. The NOAEL was considered to be 0.1 mg/kg/day for juvenile toxicity of tenapanor.

8.5 Geriatric Use

Of 1010 adult patients with CKD on dialysis randomized and treated in two randomized, double-blind, placebo-controlled randomized withdrawal clinical trials for XPHOZAH (TEN-02-201 and TEN-02-301) as well as a third randomized, double-blind, placebo-controlled trial (TEN-02-202) for XPHOZAH in combination with phosphate binders, 282 (28%) were 65 years of age and older. Clinical studies of XPHOZAH did not include sufficient numbers of patients aged 65 and older to determine whether they respond differently than younger patients.

10 OVERDOSAGE

No data are available regarding overdosage of XPHOZAH in patients. Based on nonclinical data, overdose of XPHOZAH may result in gastrointestinal adverse effects such as diarrhea, as a result of exaggerated pharmacology with a risk for dehydration if diarrhea is severe or prolonged [see Warnings and Precautions (5.1)].

11 DESCRIPTION

XPHOZAH (tenapanor) tablets contain tenapanor hydrochloride as an active ingredient. Tenapanor hydrochloride is a sodium/hydrogen exchanger 3 (NHE3) inhibitor for oral use. The chemical name for tenapanor hydrochloride is 12,15-Dioxa-2,7,9-triazaheptadecanamide, 17-[[[3-[(4S)-6,8-dichloro-1,2,3,4-tetrahydro-2-methyl-4-isoquinolinyl]phenyl]sulphonyl]amino]-N-[2-[2-[2-[[[3-[(4S)-6,8-dichloro-1,2,3,4-tetrahydro-2-methyl-4-isoquinolinyl]phenyl]sulphonyl]amino]ethoxy]ethoxy]ethyl]-8-oxo-, hydrochloride (1:2). Tenapanor hydrochloride has the molecular formula of C50H68Cl6N8O10S2, the molecular weight of 1218 Daltons, and the chemical structure below:

Tenapanor hydrochloride is a white to off-white to light brown hygroscopic amorphous solid. It is practically insoluble in water.

XPHOZAH tablets contain the equivalent of 10, 20, or 30 mg of tenapanor (provided as 10.6, 21.3, and 31.9 mg of tenapanor hydrochloride, respectively). Inactive ingredients in the tablet are colloidal silicon dioxide, low-substituted hydroxypropyl cellulose, microcrystalline cellulose, propyl gallate, stearic acid, tartaric acid, and the coating agent OPADRY®, which consists of hypromellose, titanium dioxide and triacetin, as well as iron oxide yellow as colorant [10 mg and 20 mg tablets], iron oxide red as colorant [20 mg and 30 mg tablets] and iron oxide black as colorant [30 mg tablet].

12 CLINICAL PHARMACOLOGY

12.1 Mechanism of Action

Tenapanor is a locally acting inhibitor that targets the sodium/hydrogen exchanger 3 (NHE3), an antiporter expressed on the apical surface of the epithelium of the small intestine and colon. Inhibition of NHE3 by tenapanor results in reduced sodium absorption and decreased phosphate absorption by reducing phosphate permeability through the paracellular pathway.

12.2 Pharmacodynamics

Cardiac Electrophysiology

At 3 times the mean maximum exposure of the major pharmacologically inactive metabolite of tenapanor (M1) at the recommended dosage, there were no clinically relevant effects on the QTc.

Food Effect

Administration of XPHOZAH 5 to 10 minutes before a meal increased the 24-hour stool phosphorus excretion compared to taking XPHOZAH in the fed or fasting condition [see Dosage and Administration (2.2)]. In clinical trials, XPHOZAH was administered just prior to the first meal and just prior to dinner.

Hepatic Impairment

The effect of hepatic impairment on the pharmacokinetics of XPHOZAH was studied in 20 subjects with normal or moderate hepatic impairment function (Child-Pugh B) after a single 100-mg dose. Compared to subjects with normal hepatic function, the geometric mean Cmax of the pharmacologically inactive metabolite M1, was approximately 27% to 35% lower in subjects with moderate hepatic impairment. Tenapanor exhibited minimal systemic bioavailability in subjects with both normal hepatic function and moderate hepatic impairment, with plasma concentrations below the limit of quantitation (less than 0.5 ng/mL) in the majority of samples.

12.3 Pharmacokinetics

Absorption

Tenapanor is minimally absorbed following repeated twice daily oral administration. Plasma concentrations of tenapanor were below the limit of quantitation (less than 0.5 ng/mL) in the majority of samples from subjects following single and repeated oral administration of tenapanor 30 mg twice daily. Therefore, standard pharmacokinetic parameters such as area under the curve (AUC), maximum concentration (Cmax), and half-life (t1/2) could not be determined.

Distribution

Plasma protein binding of tenapanor and its major metabolite, M1, is approximately 99% and 97%, respectively, in vitro.

Elimination

Metabolism

Tenapanor is metabolized primarily by CYP3A4/5 and low levels of its major metabolite, M1, are detected in plasma. The Cmax of M1 is approximately 3 ng/mL after a single dose of XPHOZAH 30 mg and 14 ng/mL at steady state following repeated dosing of XPHOZAH 30 mg twice daily in healthy subjects. Based on a cross-study comparison, the steady state plasma concentration of M1 in CKD patients on dialysis (eGFR less than 15 mL/min/1.73 m^2) was not notably different from those of healthy subjects given similar doses of XPHOZAH.

Excretion

Following administration of a single 15 mg radiolabeled ^14C- XPHOZAH dose to healthy subjects, approximately 70% of the radioactivity was excreted in feces through 120 hours post-dose (79% through 240 hours post-dose), mostly as the parent drug accounting for 65% of dose within 144 hours post-dose. Approximately 9% of the administered dose was recovered in urine, primarily as metabolites. M1 is excreted in urine unchanged accounting for 1.5% of dose within 144 hours post-dose.

Drug Interaction Studies

CYP Metabolism Mediated Drug Interactions

Tenapanor and M1 did not inhibit CYP1A2, CYP2B6, CYP2C8, CYP2C9, CYP2C19, and CYP2D6 in vitro.

Tenapanor and M1 did not induce CYP1A2 and CYP2B6 in vitro.

No significant inhibition or induction of CYP3A4 enzyme using midazolam as a substrate was observed when XPHOZAH 50 mg was administered twice a day for 13 days in healthy subjects.

No significant effect on PepT1 activity using cefadroxil as a substrate was observed when tenapanor 50 mg was administered twice a day for 12 days in healthy subjects.

No significant effect on P-gp and CYP2C9 activity using digoxin and warfarin as a substrate was observed when tenapanor 30 mg was administered twice a day for 12 days in healthy subjects.

Following co-administration of a single dose of XPHOZAH 50 mg with repeated doses of itraconazole 200 mg, a CYP3A4 inhibitor, the mean AUC and Cmax of M1 was decreased 50% in healthy subjects. Plasma concentrations of tenapanor were mostly below the limit of quantitation (less than 0.5 ng/mL) after co-administration of itraconazole.

Following administration of a single 20 mg enalapril dose with tenapanor (30 mg BID) at steady state, the mean AUC and Cmax of enalapril was decreased by 64% and 69%, respectively, in healthy subjects. The mean AUC and Cmax of enalaprilat was decreased by 52% and 68%, respectively, in healthy subjects.

Membrane Transporter Mediated Drug Interactions

Tenapanor inhibited OATP2B1, but is not an inhibitor of P-gp, BCRP, OATP1B1, OATP1B3, and PEPT1. M1 did not inhibit P-gp, BCRP, OATP1B1, OATP1B3, OAT1, OAT3, OCT2, MATE1, and MATE2-K.

Tenapanor is not a substrate of P-gp, BCRP, OATP1B1, and OATP1B3. M1 is a substrate of P-gp.

Interactions with Phosphate Binders

In vitro studies indicated the potential for tenapanor to bind to sevelamer carbonate but did not suggest the potential to bind to calcium carbonate or calcium acetate. In a clinical study, there did not appear to be a pharmacodynamic interaction between sevelamer carbonate (800 mg TID) and tenapanor (14 mg BID).

13 NONCLINICAL TOXICOLOGY

13.1 Carcinogenesis, Mutagenesis, Impairment of Fertility

Carcinogenesis

The carcinogenic potential of tenapanor was assessed in a 6-month carcinogenicity study in Tg rasH2 mice and in a 2-year carcinogenicity study in rats. Tenapanor was not tumorigenic at oral doses up to 100 mg/kg/day (approximately 7.5 times the recommended human dose, based on the body surface area) in male mice and 800 mg/kg/day (approximately 65 times the maximum recommended human dose, based on the body surface area) for female mice. Tenapanor was not tumorigenic in male and female rats at oral doses up to 5 mg/kg/day (approximately 0.8 times the recommended human dose, based on the body surface area). The major metabolite of tenapanor, M1, was not tumorigenic in Tg rasH2 mice at oral doses up to 165 mg/kg/day (approximately 13.3 times the maximum recommended human dose, based on the body surface area).

Mutagenesis

Tenapanor was not genotoxic in the in vitro bacterial reverse mutation (Ames) assays, an in vitro chromosomal aberration assay in cultured human peripheral blood lymphocytes or the in vivo micronucleus assays in mice and rats. The M1 metabolite of tenapanor was not genotoxic in the Ames assay and in an in vitro micronucleus assay using L5178Y cells.

Impairment of Fertility

Tenapanor had no effect on fertility or reproductive function in male rats at oral doses up to 10 mg/kg/day (approximately 1.6 times the recommended human dose, based on the body surface area) and in female mice at oral doses up to 50 mg/kg/day (approximately 4 times the recommended human dose, based on the body surface area).

14 CLINICAL STUDIES

The ability of XPHOZAH to lower serum phosphorus in adults with CKD on dialysis was evaluated in 3 trials: TEN-02-201 [NCT02675998], TEN-02-301 [NCT03427125]), and TEN-02-202 [NCT03824587]). Across these trials, the mean age of XPHOZAH-treated patients was 56 (range 24 to 88 years), 61% were males, 44% were White, 49% were Black/African American, 3% were Asian, 3% were American Indian or Alaska Native, and 1% were other.

Both monotherapy trials (TEN-02-201 and TEN-02-301) enrolled patients who, following a 3-week washout period, had an increase in serum phosphorus of at least 1.5 mg/dL (compared to pre-wash out value) and a serum phosphorus level of at least 6.0 mg/dL and not more than 10.0 mg/dL.

Study TEN-02-301

Study TEN-02-301 included a 26-week randomized, active-controlled open-label treatment period, followed by a 12-week, blinded placebo-controlled randomized withdrawal period. A total of 564 patients were randomized into the 26-week treatment period (423 to XPHOZAH and 141 to the control arm which was intended to provide controlled safety data). Among the 423 patients randomized to XPHOZAH, 255 patients (60%) completed the 26-week treatment period and were rerandomized 1:1 to remain on XPHOZAH (n=128) or receive placebo (n=127). During the randomized withdrawal phase, the phosphorus concentration rose in the placebo group by 0.7 mg/dL (95% CI: (0.2, 1.1), p=0.002) relative to patients who remained on XPHOZAH.

Study TEN-02-201

Study TEN-02-201 included an 8-week randomized, double-blind period that evaluated three dosing regimens of XPHOZAH (3 mg twice daily, 10 mg twice daily, or a titration regimen). This period was followed by a 4-week placebo-controlled randomized-withdrawal phase, during which patients were rerandomized 1:1 to their current XPHOZAH treatment or to placebo. Of the 219 patients included in the trial, 164 patients (75%) completed the 8-week randomized treatment period and were rerandomized 1:1 to receive XPHOZAH (n=82) or placebo (n=82). During the randomized withdrawal phase, the phosphorus concentration rose in the placebo group by 0.7 mg/dL (95% CI: (0.3, 1.2), p=0.003) relative to patients who remained on XPHOZAH.

Study TEN-02-202

Study TEN-02-202 was a randomized, parallel-group, double-blind, placebo-controlled study that evaluated the effect of XPHOZAH on the change in serum phosphorus when used as add-on therapy in patients on stable phosphate-binder therapy with serum phosphorus greater than or equal to 5.5 mg/dL. A total of 236 patients were randomized to receive XPHOZAH (n=117) or placebo BID (n=119) for 4 weeks. During the 4-week period, the serum phosphorus decreased by 0.7 mg/dL (95% CI: (0.3, 1.0), p=0.0004) in the add-on XPHOZAH group as compared to the add-on placebo group.

16 HOW SUPPLIED/STORAGE AND HANDLING

XPHOZAH is supplied as 10-, 20-, or 30-mg oval, biconvex, film-coated tablets supplied in white, opaque, high-density polyethylene bottles containing 60 or 14 tablets with a silica gel canister (as the desiccant) and screw-top polypropylene child-resistant cap lined with an induction-activated aluminum foil liner:

Strength | Color | Deboss | NDC
Strength | Color | Deboss | Bottle/14 | Bottle/60
10 mg | Yellow | /T10 | 73154-110-14 | 73154-110-60
20 mg | Brown | /T20 | 73154-120-14 | 73154-120-60
30 mg | Red | /T30 | 73154-130-14 | 73154-130-60

Storage

Store at 20°C to 25°C (68°F to 77°F); excursions permitted between 15°C to 30°C (59°F to 86°F) [see USP Controlled Room Temperature]. Keep bottle tightly closed to protect from moisture. Store and dispense in original bottle with the desiccant.

17 PATIENT COUNSELING INFORMATION

Advise Patients:

Diarrhea

Instruct patients to contact their healthcare provider if they experience severe diarrhea [see Warnings and Precautions (5.1)].

- Instruct patients not to use stool softeners or laxatives with XPHOZAH.

Administration and Handling Instructions

Instruct Patients:

- To take XPHOZAH just prior to the first and last meals of the day [see Dosage and Administration (2.2)].
- Patients should be counseled not to take XPHOZAH right before a hemodialysis session, and to take XPHOZAH right before the next meal, as some patients may experience diarrhea after taking XPHOZAH.
- If a dose is missed, take the dose just before the next meal. Do not take 2 doses at the same time [see Dosage and Administration (2.2)].
- To keep XPHOZAH in a dry place. Protect from moisture. Keep in the original bottle. Do not remove desiccant from the bottle. Keep bottles tightly closed [see How Supplied/Storage and Handling (16)].

Manufactured for and distributed by Ardelyx, Inc.
400 Fifth Avenue, Suite 210 Waltham, MA 02451 USA

XPHOZAH® is a registered trademark of Ardelyx, Inc.
Patent: www.XPHOZAH-patents.com

PRINCIPAL DISPLAY PANEL - 10 mg Tablet Bottle Label - NDC 73154-110-14

NDC 73154-110-14

XPHOZAH®
(tenapanor) tablets

10 mg

Attention:
Dispense and store XPHOZAH in original container
with the desiccant to protect from moisture.

14 tablets
Rx Only

PRINCIPAL DISPLAY PANEL - 10 mg Tablet Bottle Label - NDC 73154-110-60

NDC 73154-110-60

XPHOZAH®
(tenapanor) tablets

10 mg

Attention:
Dispense and store XPHOZAH in original container
with the desiccant to protect from moisture.

60 tablets
Rx Only

PRINCIPAL DISPLAY PANEL - 10 mg Tablet Bottle Label - NDC 73154-110-99

NDC 73154-110-99
PROFESSIONAL SAMPLE
NOT FOR SALE

XPHOZAH®
(tenapanor) tablets

10 mg

Attention:
Dispense and store XPHOZAH in original container
with the desiccant to protect from moisture.

14 tablets
Rx Only

PRINCIPAL DISPLAY PANEL - 20 mg Tablet Bottle Label - NDC 73154-120-14

NDC 73154-120-14

XPHOZAH®
(tenapanor) tablets

20 mg

Attention:
Dispense and store XPHOZAH in original container
with the desiccant to protect from moisture.

14 tablets
Rx Only

PRINCIPAL DISPLAY PANEL - 20 mg Tablet Bottle Label - NDC 73154-120-60

NDC 73154-120-60

XPHOZAH®
(tenapanor) tablets

20 mg

Attention:
Dispense and store XPHOZAH in original container
with the desiccant to protect from moisture.

60 tablets
Rx Only

PRINCIPAL DISPLAY PANEL - 20 mg Tablet Bottle Label - NDC 73154-120-99

NDC 73154-120-99
PROFESSIONAL SAMPLE
NOT FOR SALE

XPHOZAH®
(tenapanor) tablets

20 mg

Attention:
Dispense and store XPHOZAH in original container
with the desiccant to protect from moisture.

14 tablets
Rx Only

PRINCIPAL DISPLAY PANEL - 30 mg Tablet Bottle Label - NDC 73154-130-14

NDC 73154-130-14

XPHOZAH®
(tenapanor) tablets

30 mg

Attention:
Dispense and store XPHOZAH in original container
with the desiccant to protect from moisture.

14 tablets
Rx Only

PRINCIPAL DISPLAY PANEL - 30 mg Tablet Bottle Label - NDC 73154-130-60

NDC 73154-130-60

XPHOZAH®
(tenapanor) tablets

30 mg

Attention:
Dispense and store XPHOZAH in original container
with the desiccant to protect from moisture.

60 tablets
Rx Only

PRINCIPAL DISPLAY PANEL - 30 mg Tablet Bottle Label - NDC 73154-130-99

NDC 73154-130-99
PROFESSIONAL SAMPLE
NOT FOR SALE

XPHOZAH®
(tenapanor) tablets

30 mg

Attention:
Dispense and store XPHOZAH in original container
with the desiccant to protect from moisture.

14 tablets
Rx Only